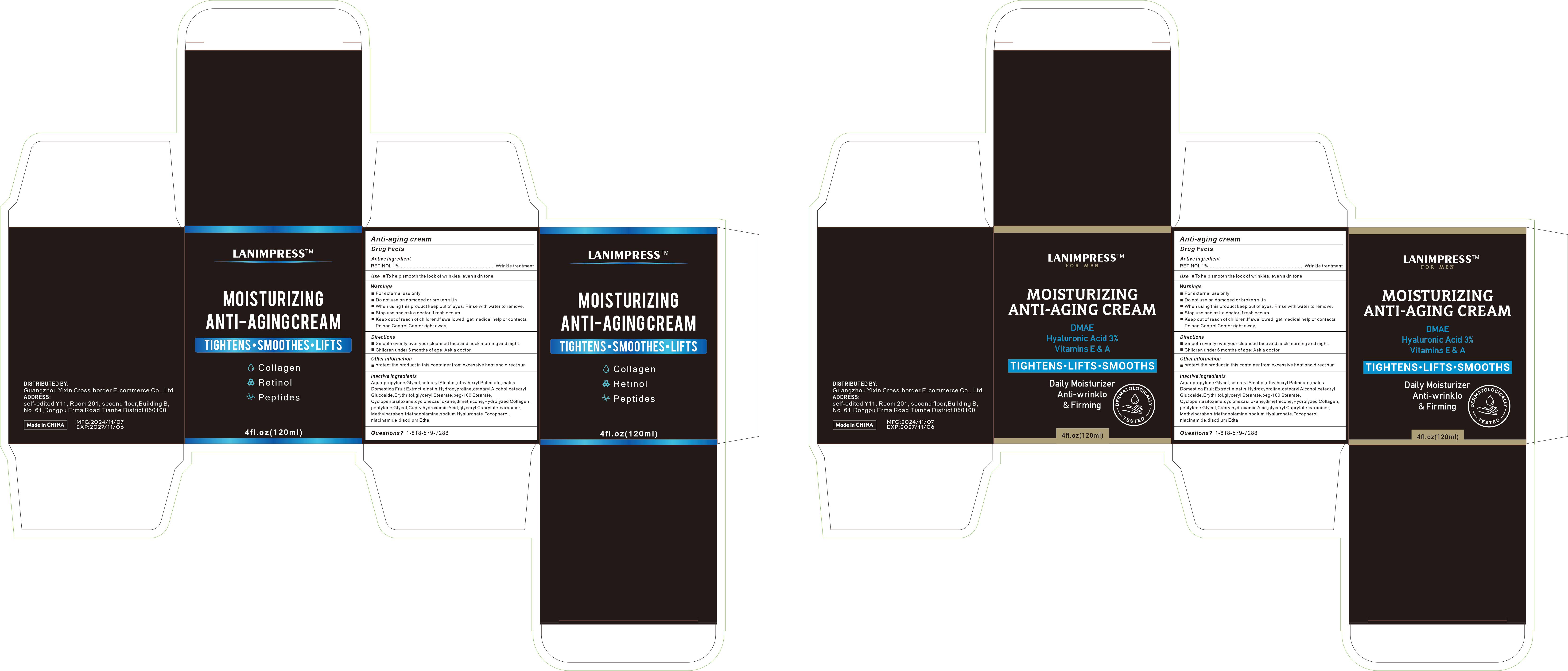 DRUG LABEL: Moisturizing Anti-Aging Cream
NDC: 84778-028 | Form: CREAM
Manufacturer: Guangzhou Yixin Cross-border E-commerce Co., Ltd.
Category: otc | Type: HUMAN OTC DRUG LABEL
Date: 20241107

ACTIVE INGREDIENTS: RETINOL 1 g/120 mL
INACTIVE INGREDIENTS: CAPRYLHYDROXAMIC ACID; ETHYLHEXYL PALMITATE; EDETATE DISODIUM; PROPYLENE GLYCOL; PENTYLENE GLYCOL; CYCLOPENTASILOXANE; GLYCERYL CAPRYLATE; HYALURONATE SODIUM; AQUA; ELASTIN; NIACINAMIDE; CETOSTEARYL ALCOHOL; GLYCERYL STEARATE; TOCOPHEROL; PEG-100 STEARATE; ERYTHRITOL; DIMETHICONE 6; PYRUS MALUS (APPLE) FRUIT; HYDROXYPROLINE; TROLAMINE; ETHYLPARABEN

COMPONENTS

RETINOL 1g

PURPOSE

To help smooth the look of wrinkles, even skin tone

INDICATIONS AND USAGE

Smooth evenly over your cleansed face and neck morning and night.

WARNINGS

For external use only

Do not use on damaged or broken skin

When using this product keep out of eyes. Rinse with water to remove.

Stop use and ask a doctor if rash occurs

Keep out of reach of children.lf swallowed, get medical help or contact a Poison Control Center right away.

DOSAGE AND ADMINISTRATION

For external use only.

Stop use and ask a doctor if rash occurs

When using this product keep out of eyes. Rinse with water to remove.

Do not use on damaged or broken skin

Keep out of reach of children.lf swallowed, get medical help or contacta Poison Control Center right away.

INACTIVE INGREDIENT

Aqua,propylene Glycol,cetearyl Alcohol, ethylhexyl Palmitate,malusDomestica Fruit Extract,elastin, Hydroxyproline,cetearyl Alcohol,cetearylGlucoside,Erythritol,glyceryl Stearate,peg-100 Stearate, pentylene Glycol,Caprylhydroxamic Acid,glyceryl Caprylate,carbomer, Methylparaben,triethanolamine,sodium Hyaluronate,Tocopherol,niacinamide,disodium EdtaCyclopentasiloxane,cyclohexasiloxane,dimethicone, Hydrolyzed Collagen,